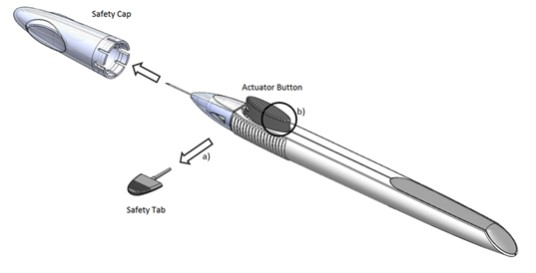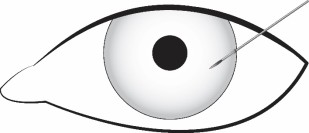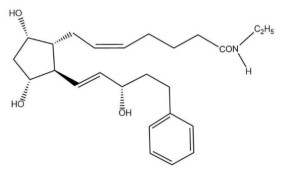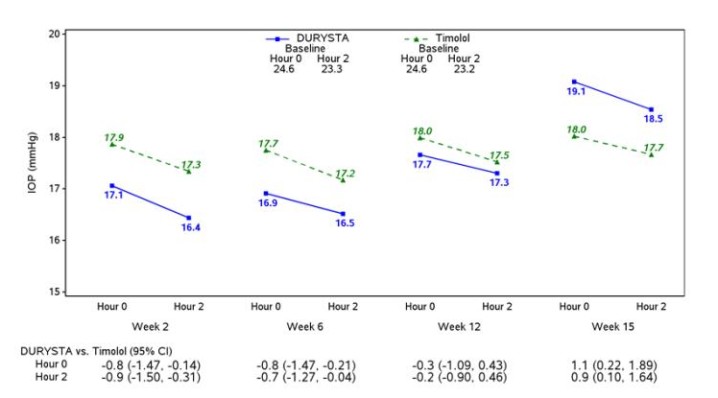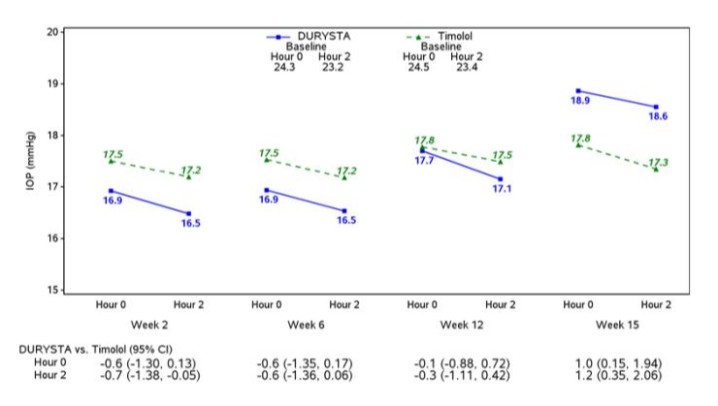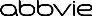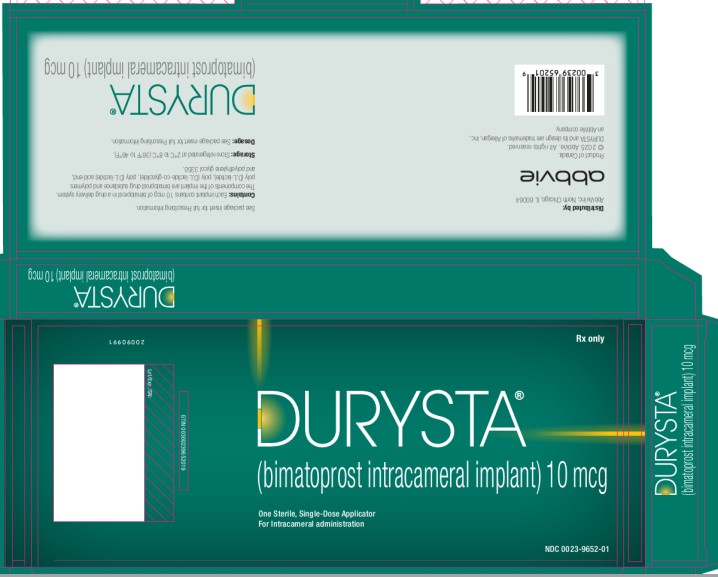 DRUG LABEL: DURYSTA
NDC: 0023-9652 | Form: IMPLANT
Manufacturer: Allergan, Inc.
Category: prescription | Type: HUMAN PRESCRIPTION DRUG LABEL
Date: 20241016

ACTIVE INGREDIENTS: BIMATOPROST 10 ug/1 1
INACTIVE INGREDIENTS: POLYLACTIDE; DL-LACTIDE AND GLYCOLIDE (50:50) COPOLYMER 12000 ACID; POLYETHYLENE GLYCOL, UNSPECIFIED

HIGHLIGHTS OF PRESCRIBING INFORMATION

These highlights do not include all the information needed to use DURYSTA safely and effectively. See full prescribing information for DURYSTA.
DURYSTA® (bimatoprost intracameral implant), for intracameral administration
Initial U.S. Approval: 2001

1 INDICATIONS AND USAGE

DURYSTA is a prostaglandin analog indicated for the reduction of intraocular pressure (IOP) in patients with open angle glaucoma (OAG) or ocular hypertension (OHT). (1)

2 DOSAGE AND ADMINISTRATION

- For ophthalmic intracameral administration. (2.1)
- The intracameral administration should be carried out under standard aseptic conditions. (2.2)

3 DOSAGE FORMS AND STRENGTHS

Intracameral implant containing bimatoprost 10 mcg, in a drug delivery system. (3)

4 CONTRAINDICATIONS

- Ocular or periocular infections (4.1)
- Corneal endothelial cell dystrophy (4.2)
- Prior corneal transplantation (4.3)
- Absent or ruptured posterior lens capsule (4.4)
- Hypersensitivity (4.5)

5 WARNINGS AND PRECAUTIONS

- Endothelial cell loss: Due to possible corneal endothelial cell loss, administration of DURYSTA should be limited to a single implant per eye without retreatment. (5.1)
- Corneal Adverse Reactions: DURYSTA has been associated with corneal adverse reactions and risks are increased with multiple implants. Use caution in patients with limited corneal endothelial cell reserve. (5.1)
- Iridocorneal Angle: DURYSTA should be used with caution in patients with narrow angles or anatomical angle obstruction. (5.2)

6 ADVERSE REACTIONS

In controlled studies, the most common ocular adverse reaction reported by 27% of patients was conjunctival hyperemia. Other common adverse reactions reported in 5-10% of patients were foreign body sensation, eye pain, photophobia, conjunctival hemorrhage, dry eye, eye irritation, intraocular pressure increased, corneal endothelial cell loss, vision blurred, iritis, and headache. (6.1)

To report SUSPECTED ADVERSE REACTIONS, contact AbbVie at 1-800-678-1605 or FDA at 1-800-FDA-1088 or www.fda.gov/medwatch.

FULL PRESCRIBING INFORMATION

1 INDICATIONS AND USAGE

DURYSTA® (bimatoprost intracameral implant) is indicated for the reduction of intraocular pressure (IOP) in patients with open angle glaucoma (OAG) or ocular hypertension (OHT).

2 DOSAGE AND ADMINISTRATION

2.1 General Information

DURYSTA is an ophthalmic drug delivery system for a single intracameral administration of a biodegradable implant. DURYSTA should not be readministered to an eye that received a prior DURYSTA.

2.2 Administration

The intracameral injection procedure must be performed under magnification that allows clear visualization of the anterior chamber structures and should be carried out using standard aseptic conditions for intracameral procedures, with the patient’s head in a stabilized position. The eye should not be dilated prior to the procedure.

Remove the foil pouch from the carton and examine for damage. Then, open the foil pouch over a sterile field and gently drop the applicator on a sterile tray. Once the foil pouch is opened, use the applicator promptly.

Figure 1

Perform a detailed visual inspection of the applicator, including ensuring that the actuator button has not been depressed, and the safety tab is in place. Carefully remove the plastic safety cap taking care to avoid contacting the needle tip. Inspect the needle tip for damage under magnification prior to use; the implant retention plug may be visible in the bevel and should not be removed.

Prior to use, remove the safety tab by pulling it out perpendicular to the long axis of the applicator (refer to Figure 1a above). Do not twist or bend the tab.

Stabilize the eye as the needle is advanced through the cornea. Enter the anterior chamber with the needle bevel visible through clear cornea. Enter parallel to the iris plane, adjacent to the limbus through clear cornea in the superotemporal quadrant.

The needle should be inserted approximately 2 bevel lengths with the bevel completely within the anterior chamber; avoid positioning the needle bevel directly over the pupil. Ensure the needle is not bent before depressing the actuator button. See Figure 2.

Figure 2

Depress the back half of the actuator button (refer to Figure 1b above) firmly until an audible and/or palpable click is noted.

Following the release of the implant, remove the needle via the same track in which it was inserted and tamponade the opening. The implant should not be left in the corneal injection track.

Check the injection site for leaks; make sure that it is self-sealing and the anterior chamber is formed.

After injection, do not recap the needle. Dispose of the used applicator in a sharps disposal container and in accordance with local requirements.

Instruct the patient to remain upright for at least 1 hour after the procedure so the implant can settle.

Some degree of eye redness and discomfort is expected following administration. However, it is recommended to instruct patients that if the eye becomes progressively red, sensitive to light, painful, or develops a change in vision, they should immediately contact the physician.

3 DOSAGE FORMS AND STRENGTHS

Intracameral implant containing 10 mcg of bimatoprost in a drug delivery system.

4 CONTRAINDICATIONS

4.1 Ocular or Periocular Infections

DURYSTA is contraindicated in patients with active or suspected ocular or periocular infections.

4.2 Corneal Endothelial Cell Dystrophy

DURYSTA is contraindicated in patients with corneal endothelial cell dystrophy (e.g., Fuchs’ Dystrophy) [see Warnings and Precautions (5.1)].

4.3 Prior Corneal Transplantation

DURYSTA is contraindicated in patients with prior corneal transplantation, or endothelial cell transplants [e.g., Descemet’s Stripping Automated Endothelial Keratoplasty (DSAEK)].

4.4 Absent or Ruptured Posterior Lens Capsule

DURYSTA is contraindicated in patients whose posterior lens capsule is absent or ruptured, due to the risk of implant migration into the posterior segment. Laser posterior capsulotomy in pseudophakic patients is not a contraindication for DURYSTA use if the intraocular lens fully covers the opening in the posterior capsule.

4.5 Hypersensitivity

DURYSTA is contraindicated in patients with hypersensitivity to bimatoprost or to any other components of the product [see Adverse Reactions (6.1)].

5 WARNINGS AND PRECAUTIONS

5.1 Corneal Adverse Reactions

The presence of DURYSTA implants has been associated with corneal adverse reactions and increased risk of corneal endothelial cell loss. Administration of DURYSTA should be limited to a single implant per eye without retreatment. Caution should be used when prescribing DURYSTA in patients with limited corneal endothelial cell reserve.

5.2 Iridocorneal Angle

Following administration with DURYSTA, the intracameral implant is intended to settle within the inferior angle. DURYSTA should be used with caution in patients with narrow iridocorneal angles (Shaffer grade ˂ 3) or anatomical obstruction (e.g., scarring) that may prohibit settling in the inferior angle.

5.3 Macular Edema

Macular edema, including cystoid macular edema, has been reported during treatment with ophthalmic bimatoprost, including DURYSTA intracameral implant. DURYSTA should be used with caution in aphakic patients, in pseudophakic patients with a torn posterior lens capsule, or in patients with known risk factors for macular edema.

5.4 Intraocular Inflammation

Prostaglandin analogs, including DURYSTA, have been reported to cause intraocular inflammation. DURYSTA should be used with caution in patients with active intraocular inflammation (e.g., uveitis) because the inflammation may be exacerbated.

5.5 Pigmentation

Ophthalmic bimatoprost, including DURYSTA intracameral implant, has been reported to cause changes to pigmented tissues, such as increased pigmentation of the iris. Pigmentation of the iris is likely to be permanent. Patients who receive treatment should be informed of the possibility of increased pigmentation. The pigmentation change is due to increased melanin content in the melanocytes rather than to an increase in the number of melanocytes. While treatment with DURYSTA can be continued in patients who develop noticeably increased iris pigmentation, these patients should be examined regularly.

5.6 Endophthalmitis

Intraocular surgical procedures and injections, including DURYSTA, have been associated with endophthalmitis. Proper aseptic technique must always be used with administering DURYSTA, and patients should be monitored following the administration.

6 ADVERSE REACTIONS

The following clinically significant adverse reactions are described elsewhere in labeling:

- Implant migration [see Contraindications (4.4)]
- Hypersensitivity [see Contraindications (4.5)]
- Corneal adverse reactions [see Warnings and Precautions (5.1)]
- Macular edema [see Warnings and Precautions (5.3)]
- Intraocular inflammation [see Warnings and Precautions (5.4)]
- Pigmentation [see Warnings and Precautions (5.5)]
- Endophthalmitis [see Warnings and Precautions (5.6)]

6.1 Clinical Trials Experience

Because clinical trials are conducted under widely varying conditions, adverse reaction rates observed in the clinical trials of a drug cannot be directly compared to rates in the clinical trials of another drug and may not reflect the rates observed in practice.

The most common ocular adverse reaction observed in two randomized, active-controlled clinical trials with DURYSTA in patients with OAG or OHT was conjunctival hyperemia, which was reported in 27% of patients. Other common ocular adverse reactions reported in 5-10% of patients were foreign body sensation, eye pain, photophobia, conjunctival hemorrhage, dry eye, eye irritation, intraocular pressure increased, corneal endothelial cell loss, vision blurred, and iritis. Ocular adverse reactions occurring in 1-5% of patients were anterior chamber cell, lacrimation increased, corneal edema, aqueous humor leakage, iris adhesions, ocular discomfort, corneal touch, iris hyperpigmentation, anterior chamber flare, anterior chamber inflammation, and macular edema. The following additional adverse drug reactions occurred in less than 1% of patients: hyphema, iridocyclitis, uveitis, corneal opacity, corneal thickening, product administered at inappropriate site, corneal decompensation, cystoid macular edema, and drug hypersensitivity.

The most common nonocular adverse reaction was headache, which was observed in 5% of patients.

6.2 Postmarketing Experience

The following adverse reactions have been identified during postapproval use of DURYSTA. Because these reactions are reported voluntarily from a population of uncertain size, it is not always possible to reliably estimate their frequency or establish a causal relationship to drug exposure.

Eye disorders: endophthalmitis

8 USE IN SPECIFIC POPULATIONS

8.1 Pregnancy

Risk Summary

There are no adequate and well-controlled studies of DURYSTA (bimatoprost intracameral implant) administration in pregnant women to inform a drug associated risk. Oral administration of bimatoprost to pregnant rats and mice throughout organogenesis did not produce adverse maternal or fetal effects at clinically relevant exposures. Oral administration of bimatoprost to rats from the start of organogenesis to the end of lactation did not produce adverse maternal, fetal or neonatal effects at clinically relevant exposures [see Animal Data].

Data

Animal Data

In an embryofetal development rat study, oral administration of bimatoprost to pregnant rats during organogenesis produced abortion at 0.6 mg/kg/day (1770-times the human systemic exposure to bimatoprost from DURYSTA, based on Cmax and a blood-to plasma partition ratio of 0.858). The No Observed Adverse Effect Level (NOAEL) for abortion was 0.3 mg/kg/day (estimated at 470-times the human systemic exposure to bimatoprost from DURYSTA, based on Cmax). No fetal abnormalities were observed at doses up to 0.6 mg/kg/day.

In an embryofetal development mouse study, oral administration of bimatoprost to pregnant mice during organogenesis produced abortion and early delivery at 0.3 mg/kg/day (2240-times the human systemic exposure to bimatoprost from DURYSTA, based on plasma Cmax level; blood-to plasma partition ratio of 0.858). The NOAEL for abortion and early delivery was 0.1 mg/kg/day (400-times the human systemic exposure to bimatoprost from DURYSTA, based on Cmax). No fetal abnormalities were observed at doses up to 0.6 mg/kg/day (5200-times the human systemic exposure to bimatoprost from DURYSTA, based on Cmax).

In a pre/postnatal development study, oral administration of bimatoprost to pregnant rats from gestation day 7 through lactation resulted in reduced gestation length, increased late resorptions, fetal deaths, and postnatal pup mortality, and reduced pup body weight at 0.3 mg/kg/day (estimated 470-times the human systemic exposure to bimatoprost from DURYSTA, based plasma Cmax and a blood-to plasma partition ratio of 0.858). No adverse effects were observed in rat offspring at 0.1 mg/kg/day (estimated 350-times the human systemic exposure to bimatoprost from DURYSTA, based on plasma Cmax).

8.2 Lactation

Risk Summary

There is no information regarding the presence of bimatoprost in human milk, the effects on the breastfed infants, or the effects on milk production. In animal studies, topical bimatoprost has been shown to be excreted in breast milk. Because many drugs are excreted in human milk, caution should be exercised when DURYSTA is administered to a nursing woman.

The developmental and health benefits of breastfeeding should be considered, along with the mother's clinical need for DURYSTA and any potential adverse effects on the breastfed child from DURYSTA.

8.4 Pediatric Use

Safety and effectiveness of DURYSTA in pediatric patients have not been established.

8.5 Geriatric Use

No overall differences in safety or effectiveness have been observed between elderly and other adult patients.

11 DESCRIPTION

DURYSTA is a sterile intracameral implant containing 10 mcg of bimatoprost, a prostaglandin analog, in a solid polymer sustained-release drug delivery system (DDS). The drug delivery system consists of poly (D,L-lactide), poly (D,L-lactide-co-glycolide), poly (D,L-lactide) acid end, and polyethylene glycol 3350. DURYSTA is preloaded into a single-use, DDS applicator to facilitate injection of the rod-shaped implant directly into the anterior chamber of the eye. The chemical name for bimatoprost is (Z)-7-[(1R,2R,3R,5S)-3,5-dihydroxy-2-[(1E,3S)-3-hydroxy-5-phenyl-1-pentenyl]cyclopentyl]-N-ethyl-5-heptenamide, and its molecular weight is 415.57. Its molecular formula is C25H37NO4. Its structural formula is:

Bimatoprost is a white to off-white powder, soluble in ethyl alcohol and methyl alcohol and slightly soluble in water. The polymer matrix slowly degrades to lactic acid and glycolic acid.

12 CLINICAL PHARMACOLOGY

12.1 Mechanism of Action

Bimatoprost, a prostaglandin analog, is a synthetic structural analog of prostaglandin with ocular hypotensive activity. Bimatoprost is believed to lower IOP in humans by increasing outflow of aqueous humor through both the trabecular meshwork (conventional) and uveoscleral routes (unconventional). Elevated IOP presents a major risk factor for glaucomatous field loss. The higher the level of IOP, the greater the likelihood of optic nerve damage and visual field loss.

12.3 Pharmacokinetics

After a single administration of DURYSTA, bimatoprost concentrations were below the lower limit of quantitation (0.001 ng/mL) in the majority (approximately 92%) of patients. The maximum bimatoprost concentration observed in any patient was 0.00224 ng/mL. Bimatoprost acid concentrations were also below the lower limit of quantitation (0.01 ng/mL) in almost all (approximately 99%) of patients.

13 NONCLINICAL TOXICOLOGY

13.1 Carcinogenesis, Mutagenesis, Impairment of Fertility

Carcinogenesis

Bimatoprost was not carcinogenic in either mice or rats when administered by oral gavage at doses up to 2 mg/kg/day and 1 mg/kg/day respectively for 104 weeks (approximately 3100 and 1700 times, respectively, the maximum human exposure [based on plasma Cmax levels; blood-to-plasma partition ratio of 0.858]).

Mutagenesis

Bimatoprost was not mutagenic or clastogenic in the Ames test, in the mouse lymphoma test, or in the in vivo mouse micronucleus tests.

Impairment of Fertility

Bimatoprost did not impair fertility in male or female rats up to doses of 0.6 mg/kg/day (1770-times the maximum human exposure, based on plasma Cmax; blood-to-plasma partition ratio of 0.858).

14 CLINICAL STUDIES

Efficacy was evaluated in two multicenter, randomized, parallel-group, controlled 20-month (including 8-month extended follow-up) studies of DURYSTA compared to twice daily topical timolol 0.5% drops, in patients with OAG or OHT. DURYSTA demonstrated an IOP reduction of approximately 5-8 mmHg in patients with a mean baseline IOP of 24.5 mmHg (see Figures 3 and 4).

Figure 3: Study 1 Mean IOP (mmHg) by Treatment Group and Treatment Difference in Mean IOP

Figure 4: Study 2 Mean IOP (mmHg) by Treatment Group and Treatment Difference in Mean IOP

16 HOW SUPPLIED/STORAGE AND HANDLING

DURYSTA contains a 10 mcg bimatoprost intracameral implant in a single-use applicator that is packaged in a sealed foil pouch containing desiccant, NDC 0023-9652-01.

Storage

Store refrigerated at 2°C to 8°C (36°F to 46°F).

17 PATIENT COUNSELING INFORMATION

Treatment-related Effects

Advise patients about the potential risk for complications including, but not limited to, the development of corneal adverse events, intraocular inflammation or endophthalmitis [see Warnings and Precautions (5.1, 5.4, 5.6)].

Potential for Pigmentation

Advise patients about the potential for increased brown pigmentation of the iris, which may be permanent [see Warnings and Precautions (5.5)].

When to Seek Physician Advice

Advise patients that if the eye becomes red, sensitive to light, painful, or develops a change in vision, they should seek immediate care from an ophthalmologist [see Warnings and Precautions (5.6)].

Distributed by: AbbVie Inc.
North Chicago, IL 60064

© 2024 AbbVie. All rights reserved.
DURYSTA and its design are trademarks of Allergan, Inc., an AbbVie company.

V2.0USPI9652

PRINCIPAL DISPLAY PANEL

NDC 0023-9652-01
DURYSTA®
(bimatoprost intracameral implant) 10 mcg
One Sterile, Single-Dose Applicator
For Intracameral administration
Rx only